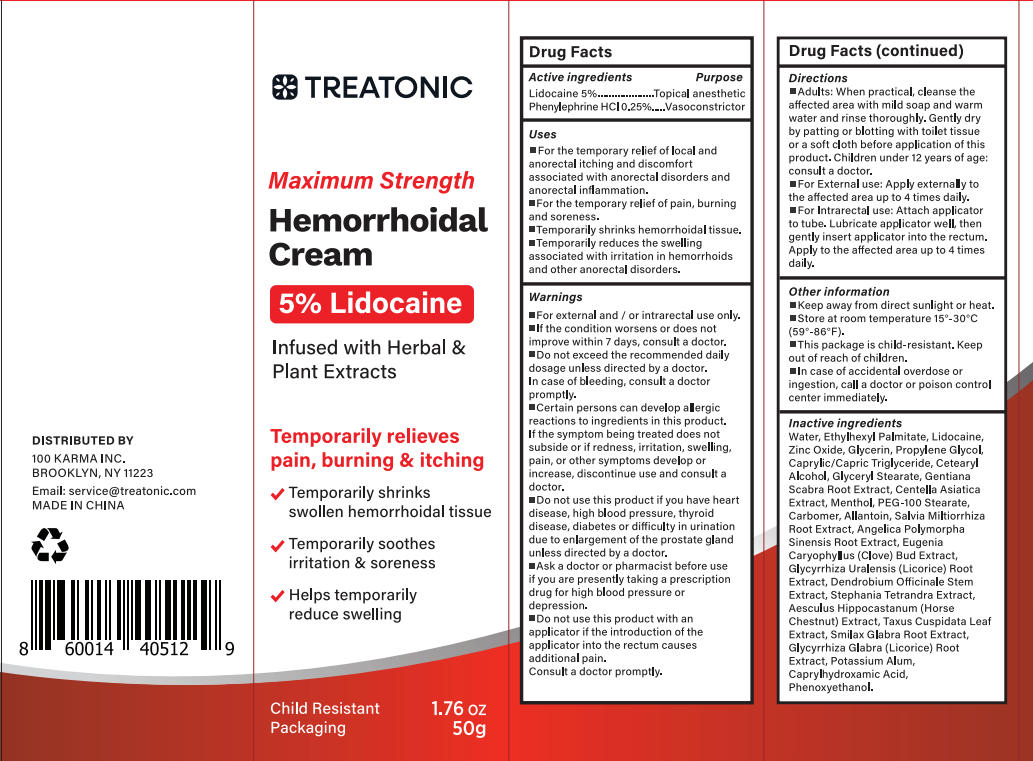 DRUG LABEL: Treatonic hemorrhoid treatment
NDC: 85569-008 | Form: CREAM
Manufacturer: 100 KARMA INC
Category: otc | Type: HUMAN OTC DRUG LABEL
Date: 20251016

ACTIVE INGREDIENTS: LIDOCAINE 2.5 g/50 g; PHENYLEPHRINE HYDROCHLORIDE 0.125 g/50 g
INACTIVE INGREDIENTS: GLYCERIN; CENTELLA ASIATICA; ANGELICA SINENSIS ROOT; CLOVE; SMILAX GLABRA WHOLE; GLYCERYL STEARATE; PEG-100 STEARATE; STEPHANIA TETRANDRA ROOT; MENTHOL; HORSE CHESTNUT; POTASSIUM ALUM; CAPRYLHYDROXAMIC ACID; CARBOMER; SALVIA MILTIORRHIZA ROOT; ETHYLHEXYL PALMITATE; ALLANTOIN; GENTIANA SCABRA ROOT; GLYCYRRHIZA URALENSIS ROOT; WATER; DENDROBIUM OFFICINALE STEM; PHENOXYETHANOL; TAXUS CUSPIDATA LEAF; ZINC OXIDE; PROPYLENE GLYCOL; CAPRYLIC/CAPRIC TRIGLYCERIDE; CETEARYL ALCOHOL; GLYCYRRHIZA GLABRA (LICORICE) ROOT

Initial Drug Listing - Treatonic hemorrhoid treatment 5% lidocaine

ACTIVE INGREDIENT

- Lidocaine 5%
- Phenylephrine HCI 0.25%

PURPOSE

- Topical anesthetic
- Vasoconstrictor

DOSAGE AND ADMINISTRATION

- For the temporary relief of local and anorectal itching and discomfort associated with anorectal disorders and anorectal inflammation.
- For the temporary reliefofpain, burning and soreness.
- Temporarily shrinks hemorrhoidal tissue.
- Temporarily reduces the swelling associated with irritation in hemorrhoids and other anorectal disorders.

WARNINGS

For external and / or intrarectal use only.

Ask a doctor or pharmacist before use if you are presently taking a prescription drug for high blood pressure or depression.

- Do not use this product if you have heart disease, high blood pressure, thyroid disease, diabetes or difficulty in urination due to enlargement of the prostate gland unless directed by a doctor.
- Do not use this product with an applicator if the introduction of the applicator into the rectum causes additional pain.
- Consult a doctor promptly.

STOP USE

- lf the condition worsens or does not improve within 7 days, consult a doctor.
- Do not exceed the recommended daily dosage unless directed by a doctor.
- In case of bleeding, consult a doctor promptly.
- Certain persons can develop allergic reactions to ingredients in this product.
- If the symptombeing treated does not subside or if redness, irritation, swelling, pain, or other symptoms develop or increase, discontinue use and consult a doctor.

Keep out of reach of children, if swallowed, get medical help or contact poison control center right away.

INDICATIONS AND USAGE

- Adults: When practical, cleanse the affected area with mild soap and warm water and rinse thoroughly. Gently dry by patting or blotting with toilet tissue or a soft cloth before application of this product. Children under 12 years of age: consult a doctor.
- For External use: Apply externally to the affected area up to 4 times daily.
- For Intrarectal use: Attach applicator to tube. Lubricate applicator well, then gently insert applicator into the rectum. Apply to the affected area up to 4 times daily.

OTHER SAFETY INFORMATION

- Keep away from direct sunlight or heat.
- Store at room temperature 15°-30°C(59°-86°F).
- This package is child-resistant. Keep out of reach of children.
- In case of accidental overdose or ingestion, call a doctor or poison control center immediately.

INACTIVE INGREDIENT

Water, Ethylhexyl Palmitate, Zinc Oxide, Glycerin, Propylene Glycol, Caprylic/Capric Triglyceride, Cetearyl Alcohol, Glyceryl Stearate, Gentiana Scabra Root Extract, Centella Asiatica Extract, Menthol, PEG-100 Stearate, Carbomer, Allantoin, Salvia Miltiorrhiza Root Extract, Angelica Polymorpha Sinensis Root Extract, Eugenia Caryophyllus (Clove) Bud Extract, Glycyrrhiza Uralensis (Licorice) Root
Extract, Dendrobium Officinale Stem Extract, Stephania Tetrandra Extract, Aesculus Hippocastanum (Horse Chestnut) Extract, Taxus Cuspidata Leaf Extract, Smilax Glabra Root Extract, Glycyrrhiza Glabra (Licorice) Root Extract, Potassium Alum, Caprylhydroxamic Acid, Phenoxyethanol.